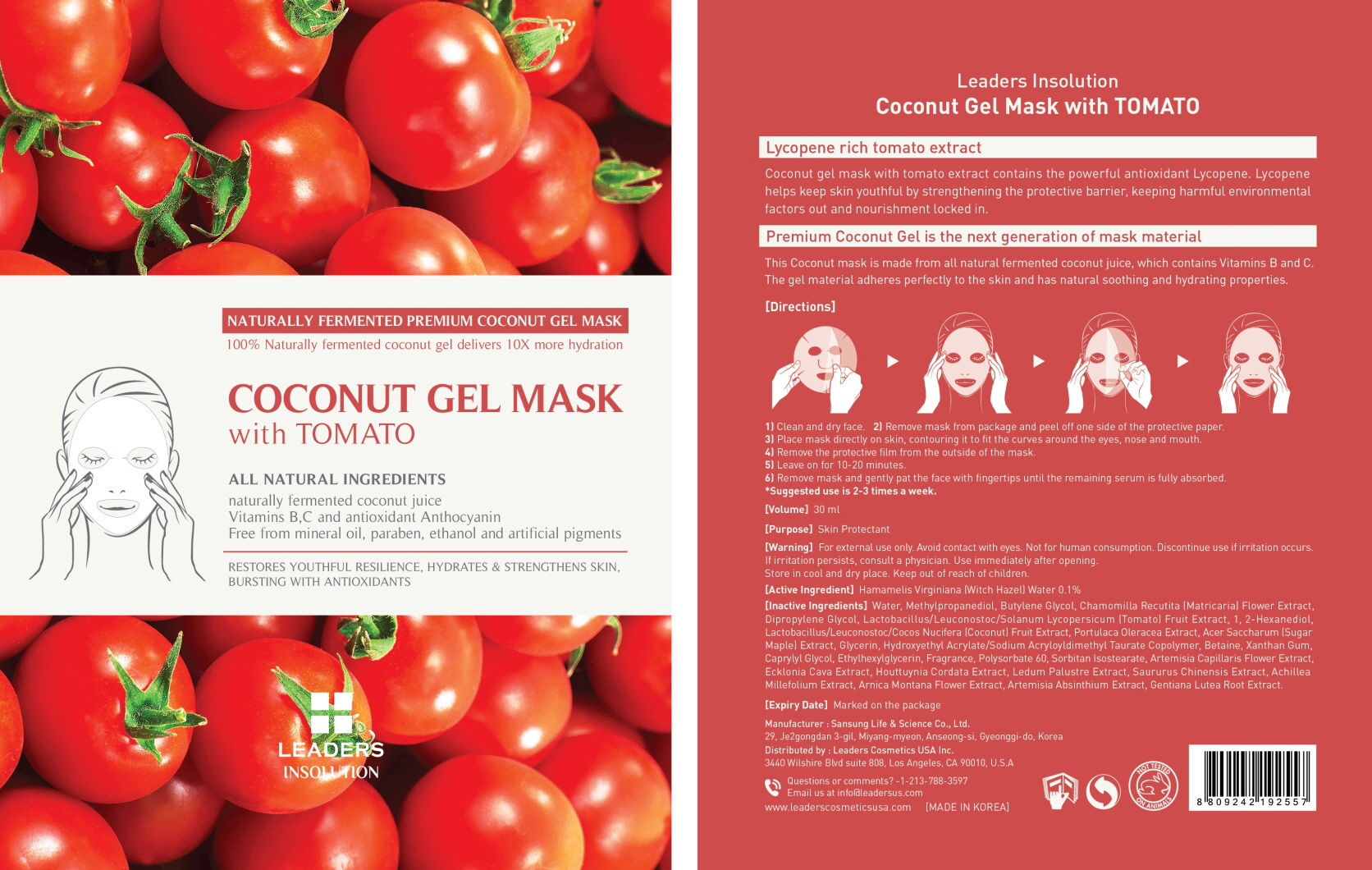 DRUG LABEL: Leaders Coconut Mask with Tomato
NDC: 69424-380 | Form: PATCH
Manufacturer: SANSUNG LIFE & SCIENCE CO., LTD.
Category: otc | Type: HUMAN OTC DRUG LABEL
Date: 20160129

ACTIVE INGREDIENTS: Witch Hazel 30 mg/30 mL
INACTIVE INGREDIENTS: Water; Methylpropanediol

ACTIVE INGREDIENT

[Active Ingredient] Hamamelis Virginiana (Witch Hazel) Water 0.1%

INACTIVE INGREDIENT

[Inactive Ingredients] Water, Methylpropanediol, Butylene Glycol, Chamomilla Recutita (Matricaria) Flower Extract, Dipropylene Glycol, Lactobacillus/Leuconostoc/Solanum Lycopersicum (Tomato) Fruit Extract, 1, 2-Hexanediol, Lactobacillus/Leuconostoc/Cocos Nucifera (Coconut) Fruit Extract, Portulaca Oleracea Extract, Acer Saccharum (Sugar Maple) Extract, Glycerin, Hydroxyethyl Acrylate/Sodium Acryloyldimethyl Taurate Copolymer, Betaine, Xanthan Gum, Caprylyl Glycol, Ethylhexylglycerin, Fragrance, Polysorbate 60, Sorbitan Isostearate, Artemisia Capillaris Flower Extract, Ecklonia Cava Extract, Houttuynia Cordata Extract, Ledum Palustre Extract, Saururus Chinensis Extract, Achillea Millefolium Extract, Arnica Montana Flower Extract, Artemisia Absinthium Extract, Gentiana Lutea Root Extract.

PURPOSE

[Purpose] Skin Protectant

WARNINGS

[Warning] For external use only. Avoid contact with eyes. Not for human consumption. Discontinue use if irritation occurs. If irritation persists, consult a physician. Use immediately after opening. Store in cool and dry place. Keep out of reach of children.

KEEP OUT OF REACH OF CHILDREN

Directions

1) Clean and dry face. 2) Remove mask from package and peel off one side of the protective paper. 3) Place mask directly on skin, contouring it to fit the curves around the eyes, nose and mouth. 4)Remove the protective film from the outside of the mask. 5) Leave on for 10-20 minutes. 6)Remove mask and gently pat the face with fingertips until the remaining serum is fully absorbed. *Suggested use is 2-3 times a week.

Directions

1) Clean and dry face. 2) Remove mask from package and peel off one side of the protective paper. 3) Place mask directly on skin, contouring it to fit the curves around the eyes, nose and mouth. 4)Remove the protective film from the outside of the mask. 5) Leave on for 10-20 minutes. 6)Remove mask and gently pat the face with fingertips until the remaining serum is fully absorbed. *Suggested use is 2-3 times a week.